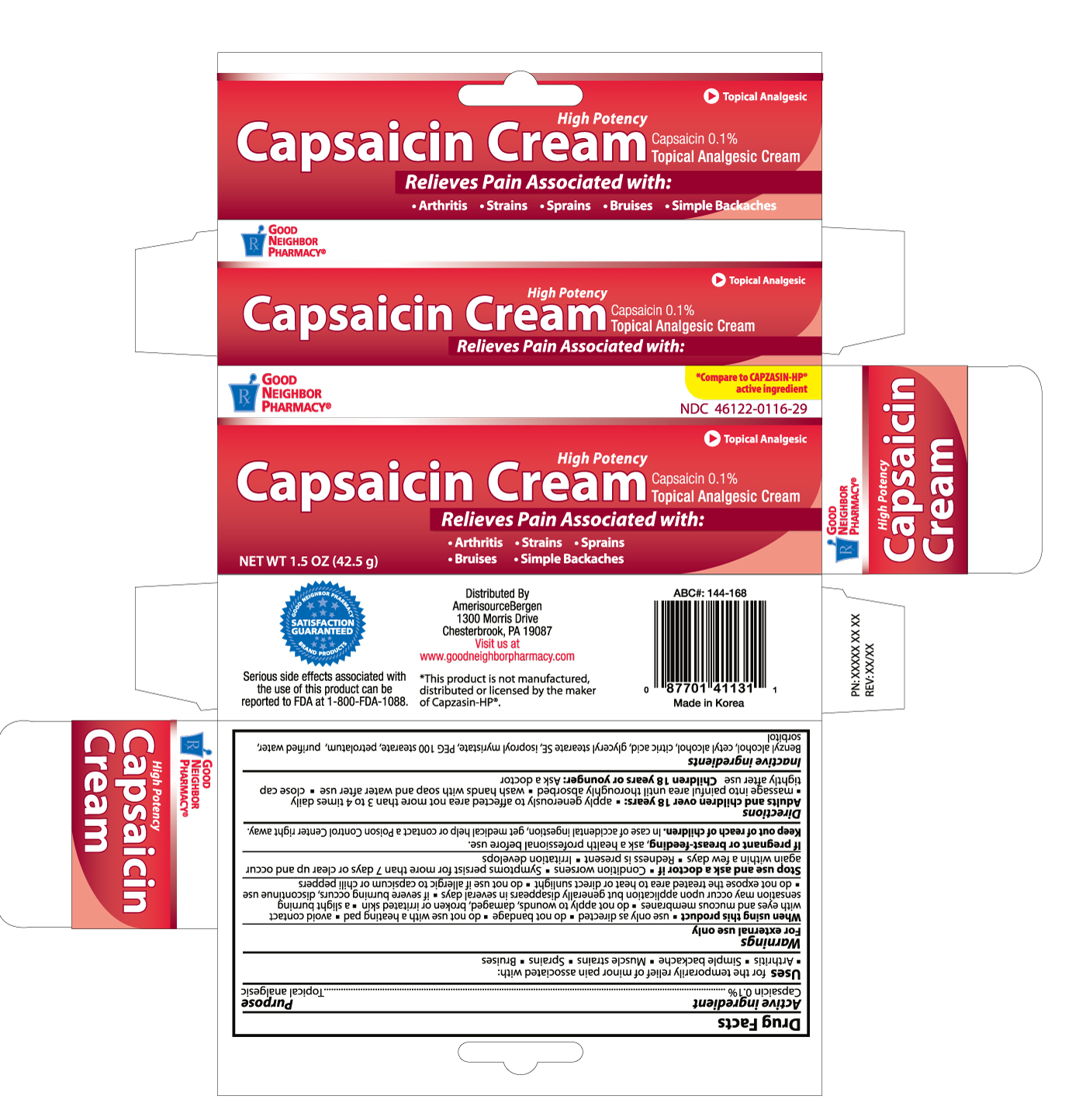 DRUG LABEL: GOOD NEIGHBOR PHARMACY CAPSAICIN
NDC: 46122-116 | Form: CREAM
Manufacturer: AMERISOURCE BERGEN
Category: otc | Type: HUMAN OTC DRUG LABEL
Date: 20120401

ACTIVE INGREDIENTS: CAPSAICIN 0.1 g/100 g
INACTIVE INGREDIENTS: BENZYL ALCOHOL; CETYL ALCOHOL; CITRIC ACID MONOHYDRATE; GLYCERYL MONOSTEARATE; ISOPROPYL MYRISTATE; PEG-100 STEARATE; PETROLATUM; WATER

Drug Facts

Active ingredient Purpose

Capsaicin 0.1%........................................................................Topical analgesic

PURPOSE

For the temporary relief of minor pain associated with:

- Arthritis
- Simple backache
- Muscle strains
- Sprains
- Bruises

Warnings

For external use only

When using this product

- use only as directed
- do not bandage
- do not use with heating pad
- avoid contact with eyes and mucous membranes
- do not apply to wounds, damaged, broken or irritated skin
- a slight burning
- sensation may occur upon application but generally disappears in several days
- if severe burning occurs, discontinue use
- do not expose the treated area to heat or direct sunlight
- do not use if allergic to capsicum or chili peppers

Stop use and ask a doctor if

- condition worsens
- symptoms persist for more than 7 days or clear up and occur again within a few days
- redness is present
- irritation develops

PREGNANCY OR BREAST FEEDING

If pregnant or breast-feeding, ask a health professional before use.

Keep out of reach of children.

In case of accidental ingestion, get medical help or contact a Poison Control Center right away.

Directions

Adults and children over 18 years:

- apply generously to affected area not more than 3 to 4 times daily
- massage into painful area until thoroughly absorbed
- wash hands with soap and water after use
- close cap tightly after use

Children 18 years or younger: Ask a doctor

Inactive ingredients

Benzyl alcohol, cetyl alcohol, citric acid, glyceryl stearate SE, isopropyl myristate, PEG 100 stearate, petrolatum, purified water, sorbitol

DOSAGE AND ADMINISTRATION

Distributed By

Amerisource Bergen

1300 Morris Drive

Chesterbrook, PA 19087

Visit us at

www.goodneighborpharmacy.com

Made in Korea

PACKAGE LABEL

Enter section text here